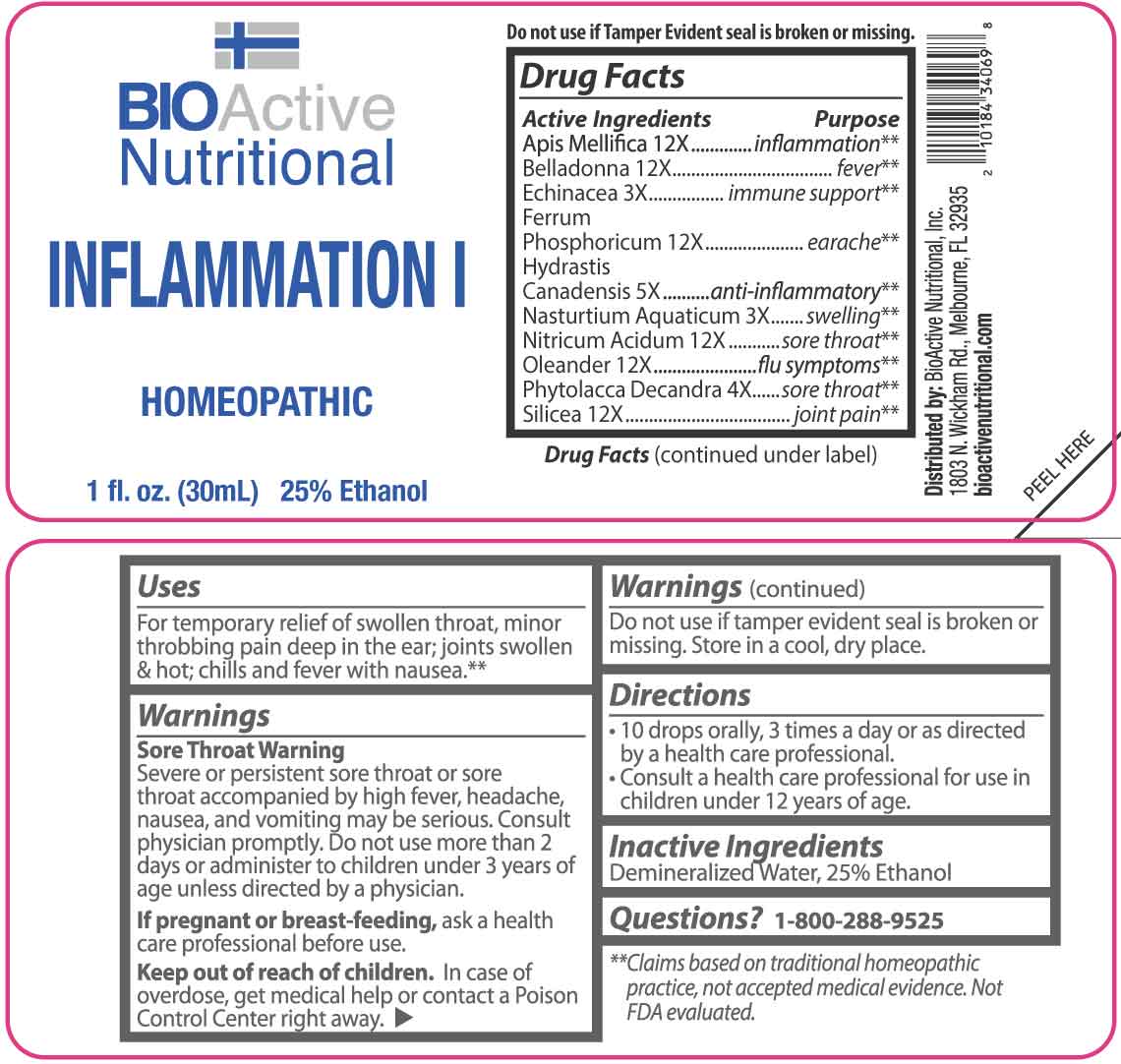 DRUG LABEL: Inflammation I
NDC: 43857-0662 | Form: LIQUID
Manufacturer: BioActive Nutritional, Inc.
Category: homeopathic | Type: HUMAN OTC DRUG LABEL
Date: 20260121

ACTIVE INGREDIENTS: ECHINACEA ANGUSTIFOLIA WHOLE 3 [hp_X]/1 mL; NASTURTIUM OFFICINALE 3 [hp_X]/1 mL; PHYTOLACCA AMERICANA ROOT 4 [hp_X]/1 mL; GOLDENSEAL 5 [hp_X]/1 mL; APIS MELLIFERA 12 [hp_X]/1 mL; ATROPA BELLADONNA 12 [hp_X]/1 mL; FERROSOFERRIC PHOSPHATE 12 [hp_X]/1 mL; NITRIC ACID 12 [hp_X]/1 mL; NERIUM OLEANDER LEAF 12 [hp_X]/1 mL; SILICON DIOXIDE 12 [hp_X]/1 mL
INACTIVE INGREDIENTS: WATER; ALCOHOL

DRUG FACTS:

ACTIVE INGREDIENTS:

Apis Mellifica 12X, Belladonna 12X, Echinacea 3X, Ferrum Phosphoricum 12X, Hydrastis Canadensis 5X, Nasturtium Aquaticum 3X, Nitricum Acidum 12X, Oleander 12X, Phytolacca Decandra 4X, Silicea 12X.

PURPOSE:

Apis Mellifica - inflammation,** Belladonna - fever,** Echinacea – immune support,** Ferrum Phosphoricum - earache,** Hydrastis Canadensis – anti-inflammatory,** Nasturtium Aquaticum - swelling,** Nitricum Acidum – sore throat,** Oleander – flu symptoms,** Phytolacca Decandra – sore throat,** Silicea – joint pain**
**Claims based on traditional homeopathic practice, not accepted medical evidence. Not FDA evaluated.

USES:

For temporary relief of swollen throat, minor throbbing pain deep in the ear; joints swollen & hot; chills and fever with nausea.**

**Claims based on traditional homeopathic practice, not accepted medical evidence. Not FDA evaluated.

WARNINGS:

Sore Throat Warning

Severe or persistent sore throat or sore throat accompanied by high fever, headache, nausea, and vomiting may be serious. Consult physician promptly. Do not use more than 2 days or administer to children under 3 years of age unless directed by physician.

If pregnant or breast-feeding, ask a health care professional before use.

Keep out of reach of children. In case of overdose, get medical help or contact a Poison Control Center right away.

Do not use if tamper evident seal is broken or missing.

Store in a cool, dry place.

KEEP OUT OF REACH OF CHILDREN:

In case of overdose, get medical help or contact a Poison Control Center right away.

DIRECTIONS:

• 10 drops orally, 3 times a day or as directed by a health care professional.

• Consult a health care professional for use in children under 12 years of age.

INACTIVE INGREDIENTS:

Demineralized Water, 25% Ethanol.

QUESTIONS:

Distributed by:

BioActive Nutritional, Inc.

1803 N. Wickham Rd.

Melbourne, FL 32935

bioactivenutritional.com

1/800-288-9525

PACKAGE LABEL DISPLAY:

BIOActive Nutritional

INFLAMMATION I

HOMEOPATHIC

1 fl. oz. (30mL)